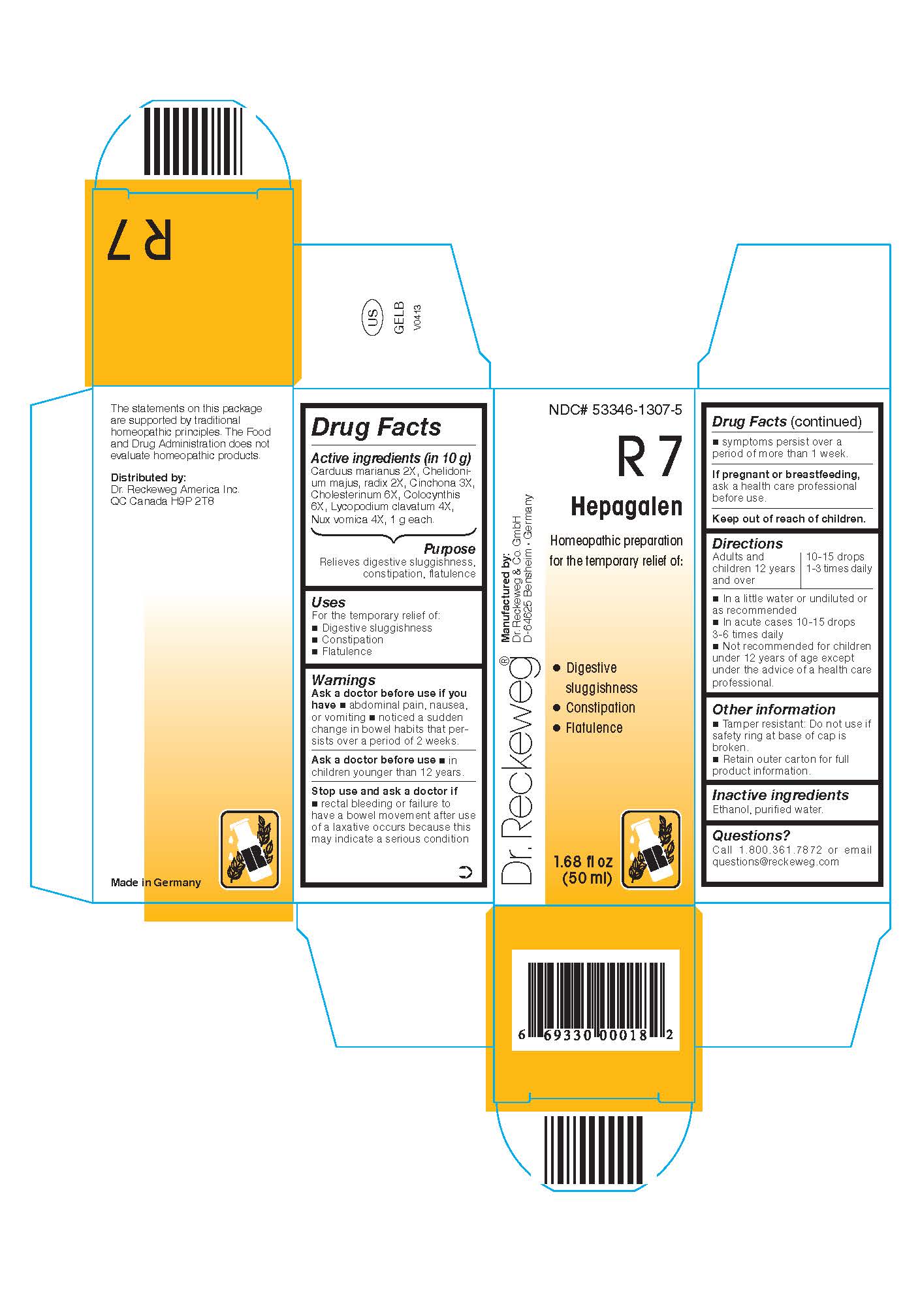 DRUG LABEL: DR. RECKEWEG R7 Hepagalen
NDC: 53346-1307 | Form: LIQUID
Manufacturer: PHARMAZEUTISCHE FABRIK DR. RECKEWEG & CO
Category: homeopathic | Type: HUMAN OTC DRUG LABEL
Date: 20130403

ACTIVE INGREDIENTS: SILYBUM MARIANUM SEED 2 [hp_X]/50 mL; CHELIDONIUM MAJUS ROOT 2 [hp_X]/50 mL; CINCHONA BARK 3 [hp_X]/50 mL; CHOLESTEROL 6 [hp_X]/50 mL; CITRULLUS COLOCYNTHIS FRUIT PULP 6 [hp_X]/50 mL; LYCOPODIUM CLAVATUM SPORE 4 [hp_X]/50 mL; STRYCHNOS NUX-VOMICA SEED 4 [hp_X]/50 mL
INACTIVE INGREDIENTS: ALCOHOL; WATER

DR. RECKEWEG R7 Hepagalen

Active ingredients

Carduus marianus 2X, Chelidonium majus, radix 2X, Cinchona 3X, Cholesterinum 6X, Colocynthis 6X, Lycopodium clavatum 4X, Nux vomica 4X, 1 g each in 10 g.

Purpose

Relieves digestive sluggishness, constipation, flatulence

Uses

For the temporary relief of:

- Digestive sluggishness
- Constipation
- Flatulence

Warnings

Ask a doctor before useif you have

- abdominal pain, nausea, or vomiting
- noticed a sudden change in bowel habits that persists over a period of 2 weeks.

Ask a doctor before use

- in children younger than 12 years.

Stop use and ask a doctor if

- rectal bleeding or failure to have a bowel movement after use of a laxative occurs because this may indicate a serious condition
- symptoms persist over a period of more than 1 week.

PREGNANCY OR BREAST FEEDING

If pregnant or breastfeeding, ask a health care professional before use.

Keep out of reach of children.

Directions

Adults and children ≥ 12 years 10-15 drops 1-3 times daily; acute cases: 10-15 drops 3-6 times daily in a little water or undiluted or as recommended.

Not recommended for children under 12 years of age except under the advice of a health care professional.

Other information
Tamper resistant: Do not use if safety ring at base of cap is broken.

Retain outer carton for full product instructions.

Inactive ingredients

Ethanol, purified water.

Questions?

Call 1-800-361-7872 or email questions@reckeweg.com

PACKAGE LABEL

NDC# 53346-1307-5

Dr. Reckeweg R7 Hepagalen

Homeopathic preparation for the temporary relief of:

- Digestive sluggishness
- Constipation
- Flatulence

Manufactured by:

Dr. Reckeweg Co. GmbH

D-64625 Bensheim

Germany

1.68 fl oz
(50 ml)